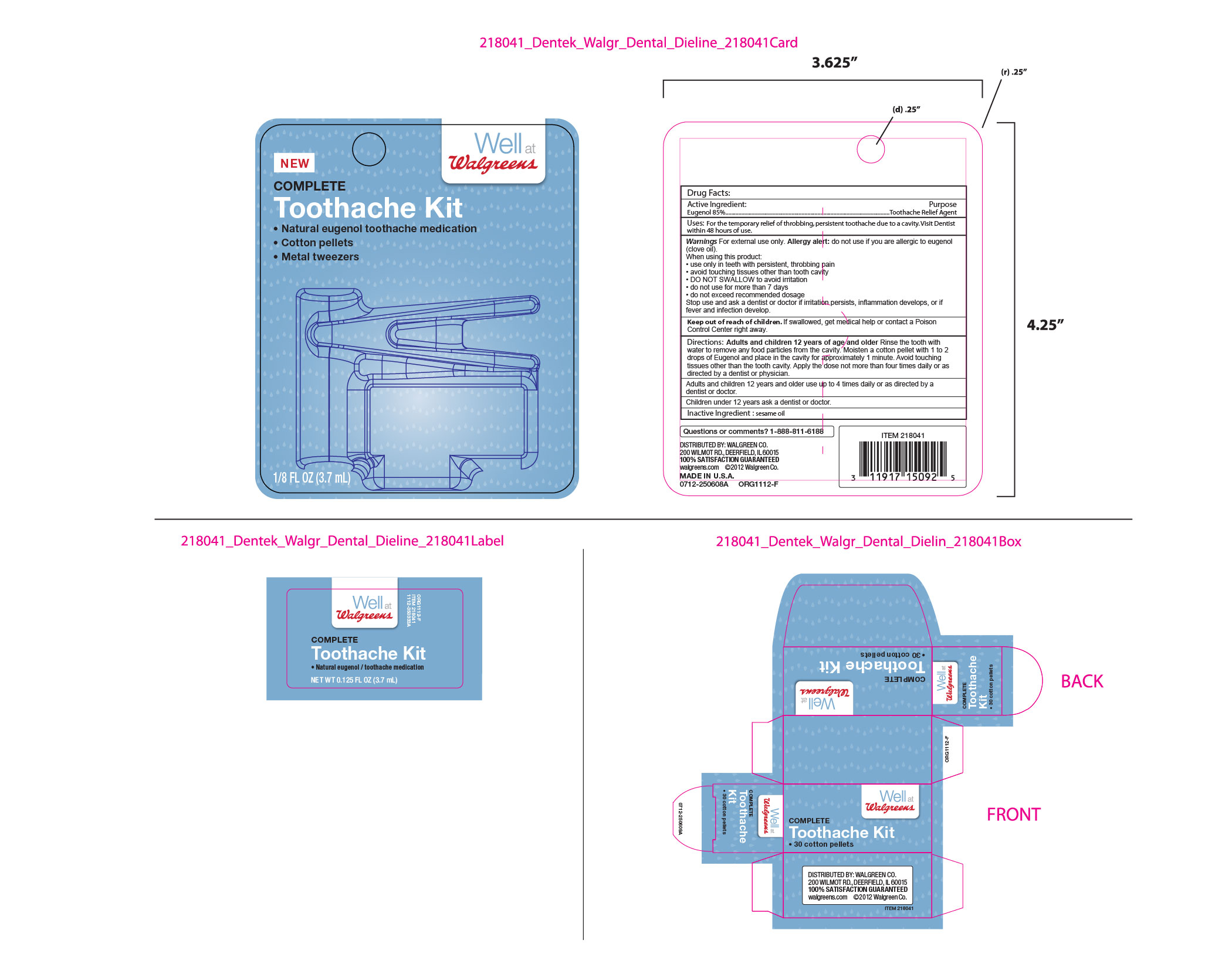 DRUG LABEL: Walgreens Natural Eugenol/Toothache Medication
NDC: 67659-405 | Form: LIQUID
Manufacturer: Team Technologies, Inc
Category: otc | Type: HUMAN OTC DRUG LABEL
Date: 20160826

ACTIVE INGREDIENTS: EUGENOL 850 mg/1 mL
INACTIVE INGREDIENTS: SESAME OIL 150 mg/1 mL

Walgreens Complete Toothache Kit, with Eugenol, cotton pellets and tweezers.

Active Ingredient:

Eugenol 85%

Purpose

Toothache Relief Agent

INDICATIONS AND USAGE

Uses: For the temporary relief of throbbing persistent toothache due to a cavity. Visit Dentist within 48 hours of use.

WARNINGS

Warnings For external use only. Allergy alert: do not use if you are allergic to eugenol (clove oil).

When using this product:

. use only in teeth with pesistent, throbbing pain

. avoid touching tissues other than tooth cavity

. DO NOT SWALLOW to avoid irritation

. do not use for more than 7 days

. do not exceed recommended dosage

Stop use and ask a dentist or doctor if irritation persists, inflammation develops, or if fever and infection develop.

Keep out of reach of children. If swallowed, get medical help or contact a Poison Control Center right away.

DOSAGE AND ADMINISTRATION

Directions: Adults and children 12 years of age and older Rinse the tooth with water to remove any food particles from the cavity.

Moisten a cotton pellet with 1 to 2 drops of Eugenol and place in the cavity for approximately 1 minute. Avoid touching tissues other than the tooth cavity. Apply the dose not more than four times daily or as directed by a dentist or physician.

Children under 12 years ask a dentist or doctor.

Inactive Ingredient: sesame oil

Questions or comments? 1-888-811-6188